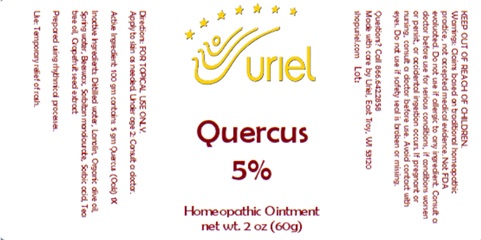 DRUG LABEL: Quercus 5
NDC: 48951-8113 | Form: OINTMENT
Manufacturer: Uriel Pharmacy Inc.
Category: homeopathic | Type: HUMAN OTC DRUG LABEL
Date: 20241106

ACTIVE INGREDIENTS: QUERCUS ROBUR WHOLE 1 [hp_X]/1 g
INACTIVE INGREDIENTS: LANOLIN; OLIVE OIL; WATER; YELLOW WAX; SORBITAN MONOLAURATE; SORBIC ACID; CITRUS PARADISI SEED; TEA TREE OIL

Quercus 5

INDICATIONS AND USAGE

Directions: FOR TOPICAL USE ONLY.

DOSAGE AND ADMINISTRATION

Apply to skin as needed. Under age 2: Consult a doctor.

Active Ingredient: 100 gm contains: 5 gm Quercus (Oak) 1X

INACTIVE INGREDIENT

Inactive Ingredients: Distilled water, Lanolin, Organic olive oil, Spring water, Beeswax, Sorbitan monolaurate, Sorbic acid, Tea tree oil, Grapefruit seed extract

Prepared using rhythmical processes

PURPOSE

Use: Temporary relief of rash.

KEEP OUT OF REACH OF CHILDREN.

Warnings: FOR EXTERNAL USE ONLY.
Do not use if allergic to any ingredient. Consult a doctor before use for serious conditions, if conditions worsen or persist, or accidental ingestion occurs. If pregnant or nursing, consult a doctor before use. Avoid contact with eyes. Do not use if safety seal is broken or missing.

QUESTIONS

Questions? Call 866.642.2858 Made with care by Uriel, East Troy, WI 53120 shopuriel.com Lot: